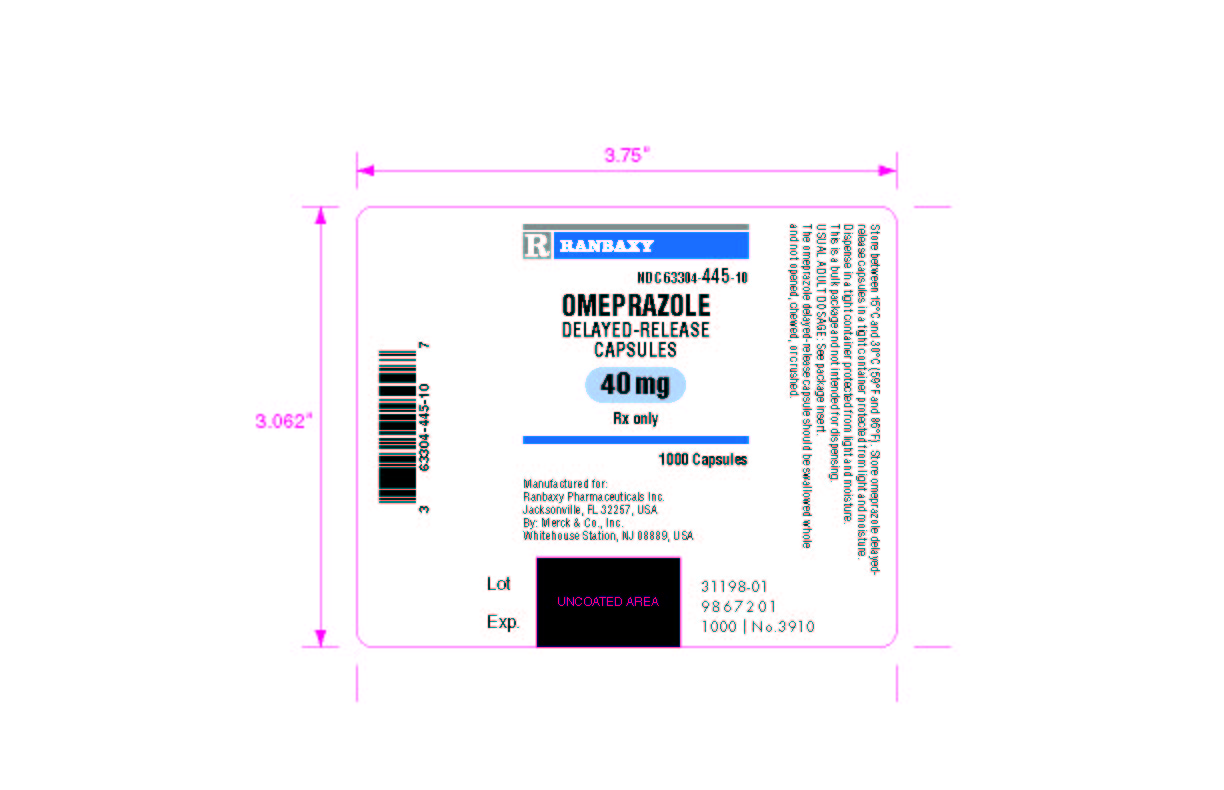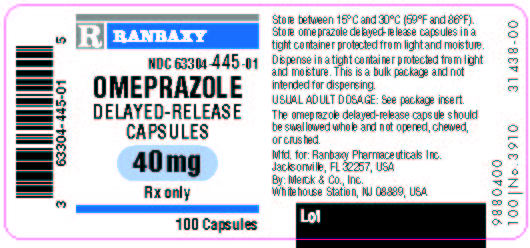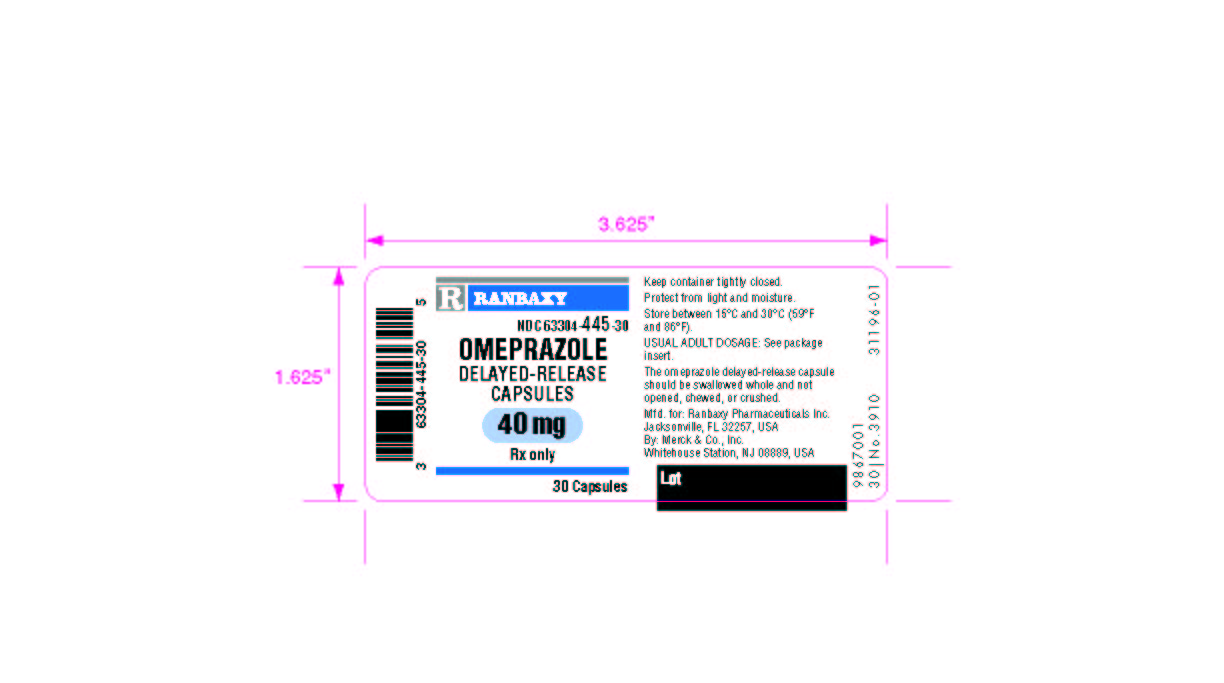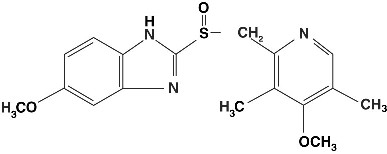 DRUG LABEL: Omeprazole Delayed-Release
NDC: 63304-445 | Form: CAPSULE, DELAYED RELEASE
Manufacturer: Ranbaxy Laboratories Inc.
Category: prescription | Type: HUMAN PRESCRIPTION DRUG LABEL
Date: 20090825

ACTIVE INGREDIENTS: OMEPRAZOLE 40 mg/1 1
INACTIVE INGREDIENTS: HYDROXYPROPYL CELLULOSE; HYPROMELLOSE; LACTOSE; MANNITOL; SODIUM LAURYL SULFATE; GELATIN; FD&C BLUE NO. 1; FD&C BLUE NO. 2; D&C RED NO. 28; D&C YELLOW NO. 10; TITANIUM DIOXIDE; BUTYL ALCOHOL; ISOPROPYL ALCOHOL; FERRIC OXIDE; CELLULOSE, MICROCRYSTALLINE

HIGHLIGHTS OF PRESCRIBING INFORMATION

These highlights do not include all the information needed to use omeprazole delayed-release capsules safely and effectively. See full prescribing information for omeprazole delayed-release capsules.
OMEPRAZOLE DELAYED-RELEASE CAPSULES
INITIAL U.S. APPROVAL: 1989

RECENT MAJOR CHANGES

Indications and Usage, Treatment of Gastroesophageal Reflux Disease (1.3) 03/2008

Dosage and Administration, Pediatric Patients (2.7) 03/2008

1 INDICATIONS AND USAGE

Omeprazole is a proton pump inhibitor indicated for:

• Treatment of duodenal ulcer in adults (1.1)

• Treatment of gastric ulcer in adults (1.2)

• Treatment of gastroesophageal reflux disease (GERD) in pediatric patients and adults (1.3)

• Maintenance of healing of erosive esophagitis in pediatric patients and adults (1.4)

• Treatment of pathological hypersecretory conditions in adults (1.5)

The safety and effectiveness of omeprazole delayed-release capsules in pediatric patients < 1 year of age have not been established. (8.4)

2 DOSAGE AND ADMINISTRATION

Indication | Omeprazole Dose |  | Frequency
Short-Term Treatment of Active Duodenal Ulcer (2.1) | 20 mg |  | Once daily for 4 weeks. Some patients may require an additional 4 weeks
H. pylori Eradication to Reduce the Risk of Duodenal Ulcer Recurrence (2.2)
Triple Therapy:
Omeprazole | 20 mg |  | Each drug twice daily for 10 days
Amoxicillin | 1000 mg
Clarithromycin | 500 mg
Dual Therapy:
Omeprazole | 40 mg |  | Once daily for 14 days
Clarithromycin | 500 mg |  | Three times daily for 14 days
Gastric Ulcer (2.3) | 40 mg |  | Once daily for 4 to 8 weeks
GERD (2.4) | 20 mg |  | Once daily for 4 to 8 weeks
Maintenance of Healing of Erosive Esophagitis (2.5) | 20 mg |  | Once daily
Pathological Hypersecretory Conditions (2.6) | 60 mg (varies with individual patient) |  | Once daily
Pediatric Patients (1 to 16 years of age) (2.7) GERDand Maintenance of Healing of Erosive Esophagitis | Weight 5 < 10 kg 10 < 20 kg > 20 kg | Dose 5 mg 10 mg 20 mg | Once daily

3 DOSAGE FORMS AND STRENGTHS

- Omeprazole Delayed-Release Capsules, 40 mg (3)

4 CONTRAINDICATIONS

Known hypersensitivity to any component of the formulation (4)

5 WARNINGS AND PRECAUTIONS

- Concomitant Gastric Malignancy: Symptomatic response to therapy with omeprazole delayed-release capsules does not preclude the presence of gastric malignancy (5.1)
- Atrophic Gastritis: Has been observed in gastric corpus biopsies from patients treated long-term with omeprazole delayed-release capsules (5.2)
- Combination Use with Clarithromycin and/or Amoxicillin: Refer to full prescribing information for individual drugs when used in combination (5.3, 5.4)

6 ADVERSE REACTIONS

Adults: Most common adverse reactions (incidence > 2%) are:

- Headache, abdominal pain, nausea, diarrhea, vomiting, and flatulence. (6)

Pediatric patients (1 to 16 years of age):

- Safety profile similar to that in adults, except that respiratory system events and fever were the most frequently reported reactions in pediatric studies (8.4)

To report SUSPECTED ADVERSE REACTIONS, contact AstraZeneca at 1-800-236-9933 or FDA at 1-800-FDA-1088 or www.fda.gov/medwatch.

7 DRUG INTERACTIONS

- Drugs for which gastric pH can affect bioavailability (e.g., ketoconazole, ampicillin esters, iron salts): Omeprazole delayed-release capsules may interfere with absorption due to inhibition of gastric acid secretion (7)
- Drugs metabolized by cytochrome P450 (e.g., diazepam, warfarin, phenytoin, cyclosporine, disulfiram, benzodiazepines): Omeprazole delayed-release capsules can prolong their elimination. Monitor to determine need for possible dose adjustments when taken with omeprazole delayed-release capsules (7)
- Patients treated with proton pump inhibitors and warfarin concomitantly may need to be monitored for increases in INR and prothrombin time (7)
- Voriconazole: May increase plasma levels of omeprazole (7)
- Atazanavir: Omeprazole delayed-release capsules may reduce plasma levels of atazanavir (7)
- Tacrolimus: Omeprazole delayed-release capsules may increase serum levels of tacrolimus (7)

8 USE IN SPECIFIC POPULATIONS

Hepatic Impairment:

- Consider dose reduction, particularly for maintenance of healing of erosive esophagitis (12.3)

Asian Patients:

- Consider dose reduction, particularly for maintenance of healing of erosive esophagitis (12.3)

FULL PRESCRIBING INFORMATION

1 INDICATIONS AND USAGE

1.1 Duodenal Ulcer (adults)

Omeprazole delayed-release capsules is indicated for short-term treatment of active duodenal ulcer in adults. Most patients heal within four weeks. Some patients may require an additional four weeks of therapy.

Omeprazole delayed-release capsules in combination with clarithromycin and amoxicillin, is indicated for treatment of patients with H. pylori infection and duodenal ulcer disease (active or up to 1-year history) to eradicate H. pylori in adults.

Omeprazole delayed-release capsules in combination with clarithromycin is indicated for treatment of patients with H. pylori infection and duodenal ulcer disease to eradicate H. pylori in adults.

Eradication of H. pylori has been shown to reduce the risk of duodenal ulcer recurrence [see Clinical Studies (14.1) and Dosage and Administration (2)].

Among patients who fail therapy, omeprazole delayed-release capsules with clarithromycin is more likely to be associated with the development of clarithromycin resistance as compared with triple therapy. In patients who fail therapy, susceptibility testing should be done. If resistance to clarithromycin is demonstrated or susceptibility testing is not possible, alternative antimicrobial therapy should be instituted. [ See Microbiology section (12.4)], and the clarithromycin package insert, Microbiology section.)

1.2 Gastric Ulcer (adults)

Omeprazole delayed-release capsules are indicated for short-term treatment (4-8 weeks) of active benign gastric ulcer in adults. [ See Clinical Studies (14.2)]

1.3 Treatment of Gastroesophageal Reflux Disease (GERD) (adults and pediatric patients)

Symptomatic GERD

Omeprazole delayed-release capsules are indicated for the treatment of heartburn and other symptoms associated with GERD in pediatric patients and adults.

Erosive Esophagitis

Omeprazole delayed-release capsules are indicated for the short-term treatment (4-8 weeks) of erosive esophagitis that has been diagnosed by endoscopy in pediatric patients and adults. [ See Clinical Studies (14.4)]

The efficacy of omeprazole delayed-release capsules used for longer than 8 weeks in these patients has not been established. If a patient does not respond to 8 weeks of treatment, an additional 4 weeks of treatment may be given. If there is recurrence of erosive esophagitis or GERD symptoms (eg, heartburn), additional 4-8 week courses of omeprazole may be considered.

1.4 Maintenance of Healing of Erosive Esophagitis (adults and pediatric patients)

Omeprazole delayed-release capsules are indicated to maintain healing of erosive esophagitis in pediatric patients and adults.

Controlled studies do not extend beyond 12 months. [ See Clinical Studies (14.4)]

1.5 Pathological Hypersecretory Conditions (adults)

Omeprazole delayed-release capsules are indicated for the long-term treatment of pathological hypersecretory conditions (eg, Zollinger-Ellison syndrome, multiple endocrine adenomas and systemic mastocytosis) in adults.

2 DOSAGE AND ADMINISTRATION

Omeprazole delayed-release capsules should be taken before eating. In the clinical trials, antacids were used concomitantly with omeprazole delayed-release capsules.

Patients should be informed that the omeprazole delayed-release capsule should be swallowed whole.

For patients unable to swallow an intact capsule, alternative administration options are available [ See Dosage and Administration (2.8)].

2.1 Short-Term Treatment of Active Duodenal Ulcer

The recommended adult oral dose of omeprazole delayed-release capsules is 20 mg once daily. Most patients heal within four weeks. Some patients may require an additional four weeks of therapy.

2.2 H. pylori Eradication for the Reduction of the Risk of Duodenal Ulcer Recurrence

Triple Therapy (omeprazole delayed-release capsules/clarithromycin/amoxicillin)-The recommended adult oral regimen is omeprazole delayed-release capsules 20 mg plus clarithromycin 500 mg plus amoxicillin 1000 mg each given twice daily for 10 days. In patients with an ulcer present at the time of initiation of therapy, an additional 18 days of omeprazole delayed-release capsules 20 mg once daily is recommended for ulcer healing and symptom relief.

Dual Therapy (omeprazole delayed-release capsules/clarithromycin)-The recommended adult oral regimen is omeprazole delayed-release capsules 40 mg once daily plus clarithromycin 500 mg three times daily for 14 days. In patients with an ulcer present at the time of initiation of therapy, an additional 14 days of omeprazole delayed-release capsules 20 mg once daily is recommended for ulcer healing and symptom relief.

2.3 Gastric Ulcer

The recommended adult oral dose is 40 mg once daily for 4-8 weeks.

2.4 Gastroesophageal Reflux Disease (GERD)

The recommended adult oral dose for the treatment of patients with symptomatic GERD and no esophageal lesions is 20 mg daily for up to 4 weeks. The recommended adult oral dose for the treatment of patients with erosive esophagitis and accompanying symptoms due to GERD is 20 mg daily for 4 to 8 weeks.

2.5 Maintenance of Healing of Erosive Esophagitis

The recommended adult oral dose is 20 mg daily. [ See Clinical Studies (14.4)]

2.6 Pathological Hypersecretory Conditions

The dosage of omeprazole delayed-release capsules in patients with pathological hypersecretory conditions varies with the individual patient. The recommended adult oral starting dose is 60 mg once daily. Doses should be adjusted to individual patient needs and should continue for as long as clinically indicated. Doses up to 120 mg three times daily have been administered. Daily dosages of greater than 80 mg should be administered in divided doses. Some patients with Zollinger-Ellison syndrome have been treated continuously with omeprazole delayed-release capsules for more than 5 years.

2.7 Pediatric Patients

For the treatment of GERD and maintenance of healing of erosive esophagitis, the recommended daily dose for pediatric patients 1 to 16 years of age is as follows:

Patient Weight | Omeprazole Daily Dose
5 < 10 kg | 5 mg
10 < 20 kg | 10 mg
≥ 20 kg | 20 mg

On a per kg basis, the doses of omeprazole required to heal erosive esophagitis in pediatric patients are greater than those for adults.

Alternative administrative options can be used for pediatric patients unable to swallow an intact capsule [s ee Dosage and Administration (2.8)].

2.8 Alternative Administration Options

Omeprazole delayed-release capsules are available as a delayed-release capsule.

For patients who have difficulty swallowing capsules, the contents of a omeprazole delayed-release capsule can be added to applesauce. One tablespoon of applesauce should be added to an empty bowl and the capsule should be opened. All of the pellets inside the capsule should be carefully emptied on the applesauce. The pellets should be mixed with the applesauce and then swallowed immediately with a glass of cool water to ensure complete swallowing of the pellets. The applesauce used should not be hot and should be soft enough to be swallowed without chewing. The pellets should not be chewed or crushed. The pellets/applesauce mixture should not be stored for future use.

3 DOSAGE FORMS AND STRENGTHS

Omeprazole delayed-release capsules, 40 mg, are opaque, hard gelatin, apricot and amethyst colored capsules, coded 1740 on cap and 40 mg on the body.

4 CONTRAINDICATIONS

Omeprazole delayed-release capsules are contraindicated in patients with known hypersensitivity to any component of the formulation. Hypersensitivity reactions may include anaphylaxis, anaphylactic shock, angioedema, bronchospasm, interstitial nephritis, and urticaria [ see Adverse Reactions (6)].

5 WARNINGS AND PRECAUTIONS

5.1 Concomitant Gastric Malignancy

Symptomatic response to therapy with omeprazole does not preclude the presence of gastric malignancy.

5.2 Atrophic Gastritis

Atrophic gastritis has been noted occasionally in gastric corpus biopsies from patients treated long-term with omeprazole.

5.3 Combination Use of Omeprazole Delayed-Release Capsules with Amoxicillin

Serious and occasionally fatal hypersensitivity (anaphylactic) reactions have been reported in patients on penicillin therapy. These reactions are more likely to occur in individuals with a history of penicillin hypersensitivity and/or a history of sensitivity to multiple allergens. Before initiating therapy with amoxicillin, careful inquiry should be made concerning previous hypersensitivity reactions to penicillins, cephalosporins or other allergens. If an allergic reaction occurs, amoxicillin should be discontinued and appropriate therapy instituted. Serious anaphylactic reactions require immediate emergency treatment with epinephrine. Oxygen, intravenous steroids and airway management, including intubation, should also be administered as indicated.

Pseudomembranous colitis has been reported with nearly all antibacterial agents and may range in severity from mild to life-threatening. Therefore, it is important to consider this diagnosis in patients who present with diarrhea subsequent to the administration of antibacterial agents.

Treatment with antibacterial agents alters the normal flora of the colon and may permit overgrowth of clostridia. Studies indicate that a toxin produced by Clostridium difficile is a primary cause of “antibiotic-associated colitis.”

After the diagnosis of pseudomembranous colitis has been established, therapeutic measures should be initiated. Mild cases of pseudomembranous colitis usually respond to discontinuation of the drug alone. In moderate to severe cases, consideration should be given to management with fluids and electrolytes, protein supplementation, and treatment with an antibacterial drug clinically effective against Clostridium difficile colitis.

5.4 Combination Use of Omeprazole Delayed-Release Capsules with Clarithromycin

Clarithromycin should not be used in pregnant women except in clinical circumstances where no alternative therapy is appropriate. If pregnancy occurs while taking clarithromycin, the patient should be apprised of the potential hazard to the fetus. (See Warnings in prescribing information for clarithromycin.)

Co-administration of omeprazole and clarithromycin has resulted in increases in plasma levels of omeprazole, clarithromycin, and 14-hydroxy-clarithromycin. [ See Clinical Pharmacology (12)]

Concomitant administration of clarithromycin with cisapride or pimozide, is contraindicated.

6 ADVERSE REACTIONS

6.1 Clinical Trials Experience with Omeprazole Delayed-Release Capsules Monotherapy

Because clinical trials are conducted under widely varying conditions, adverse reaction rates observed in the clinical trials of a drug cannot be directly compared to rates in the clinical trials of another drug and may not reflect the rates observed in practice.

The safety data described below reflects exposure to omeprazole delayed-release capsules in 3096 patients from worldwide clinical trials (465 patients from US studies and 2,631 patients from international studies). Indications clinically studied in US trials included duodenal ulcer, resistant ulcer, and Zollinger-Ellison syndrome. The international clinical trials were double blind and open-label in design. The most common adverse reactions reported (i.e., with an incidence rate ≥ 2%) from omeprazole delayed-release capsule-treated patients enrolled in these studies included headache (6.9%), abdominal pain (5.2%), nausea (4.0%), diarrhea (3.7%), vomiting (3.2%), and flatulence (2.7%).

Additional adverse reactions that were reported with an incidence ≥ 1% included acid regurgitation (1.9%), upper respiratory infection (1.9%), constipation (1.5%), dizziness (1.5%), rash (1.5%), asthenia (1.3%), back pain (1.1%), and cough (1.1%).

The clinical trial safety profile in patients greater than 65 years of age was similar to that in patients 65 years of age or less.

The clinical trial safety profile in pediatric patients who received omeprazole delayed-release capsules was similar to that in adult patients. Unique to the pediatric population, however, adverse reactions of the respiratory system were most frequently reported in both the 1 to < 2 and 2 to 16 year age groups (75.0% and 18.5%, respectively). Similarly, fever was frequently reported in the 1 to 2 year age group (33.0%), and accidental injuries were reported frequently in the 2 to 16 year age group (3.8%). [ See Use in Specific Populations (8.4)]

6.2 Clinical Trials Experience with Omeprazole Delayed-Release Capsules in Combination Therapy for H. pylori Eradication

In clinical trials using either dual therapy with omeprazole delayed-release capsules and clarithromycin, or triple therapy with omeprazole delayed-release capsules, clarithromycin, and amoxicillin, no adverse reactions unique to these drug combinations were observed. Adverse reactions observed were limited to those previously reported with omeprazole, clarithromycin, or amoxicillin alone.

Dual Therapy (omeprazole delayed-release capsules/clarithromycin)

Adverse reactions observed in controlled clinical trials using combination therapy with omeprazole delayed-release capsules and clarithromycin (n = 346) that differed from those previously described for omeprazole delayed-release capsules alone were taste perversion (15%), tongue discoloration (2%), rhinitis (2%), pharyngitis (1%) and flu-syndrome (1%). (For more information on clarithromycin, refer to the clarithromycin prescribing information, Adverse Reactions section).

Triple Therapy (omeprazole delayed-release capsules/clarithromycin/amoxicillin)

The most frequent adverse reactions observed in clinical trials using combination therapy with omeprazole delayed-release capsules, clarithromycin, and amoxicillin (n = 274) were diarrhea (14%), taste perversion (10%), and headache (7%). None of these occurred at a higher frequency than that reported by patients taking antimicrobial agents alone. (For more information on clarithromycin or amoxicillin, refer to the respective prescribing information, Adverse Reactions sections).

6.3 Post-marketing Experience

The following adverse reactions have been identified during post-approval use of omeprazole delayed-release capsules. Because these reactions are voluntarily reported from a population of uncertain size, it is not always possible to reliably estimate their actual frequency or establish a causal relationship to drug exposure.

Body Asa Whole: Hypersensitivity reactions including anaphylaxis, anaphylactic shock, angioedema, bronchospasm, interstitial nephritis, urticaria, (see also Skin below); fever; pain; fatigue; malaise;

Cardiovascular: Chest pain or angina, tachycardia, bradycardia, palpitations, elevated blood pressure, peripheral edema

Endocrine: Gynecomastia

Gastrointestinal: Pancreatitis (some fatal), anorexia, irritable colon, fecal discoloration, esophageal candidiasis, mucosal atrophy of the tongue, stomatitis, abdominal swelling, dry mouth. During treatment with omeprazole, gastric fundic gland polyps have been noted rarely. These polyps are benign and appear to be reversible when treatment is discontinued.

Gastroduodenal carcinoids have been reported in patients with ZE syndrome on long-term treatment with omeprazole delayed-release capsules. This finding is believed to be a manifestation of the underlying condition, which is known to be associated with such tumors.

Hepatic: Liver disease including hepatic failure (some fatal), liver necrosis (some fatal), hepatic encephalopathy hepatocellular disease, cholestatic disease, mixed hepatitis, jaundice, and elevations of liver function tests [ALT, AST, GGT, alkaline phosphatase, and bilirubin]

Metabolic/Nutritional: Hypoglycemia, hyponatremia, weight gain

Musculoskeletal: Muscle weakness, myalgia, muscle cramps, joint pain, leg pain

Nervous System/Psychiatric: Psychiatric and sleep disturbances including depression, agitation, aggression, hallucinations, confusion, insomnia, nervousness, apathy, somnolence, anxiety, and dream abnormalities; tremors, paresthesia; vertigo

Respiratory: Epistaxis, pharyngeal pain

Skin: Severe generalized skin reactions including toxic epidermal necrolysis (some fatal), Stevens-Johnson syndrome, and erythema multiforme; photosensitivity; urticaria; rash; skin inflammation; pruritus; petechiae; purpura; alopecia; dry skin; hyperhidrosis

Special Senses: Tinnitus, taste perversion

Ocular: Optic atrophy, anterior ischemic optic neuropathy, optic neuritis, dry eye syndrome, ocular irritation, blurred vision, double vision

Urogenital: Interstitial nephritis, hematuria, proteinuria, elevated serum creatinine, microscopic pyuria, urinary tract infection, glycosuria, urinary frequency, testicular pain

Hematologic: Agranulocytosis (some fatal), hemolytic anemia, pancytopenia, neutropenia, anemia, thrombocytopenia, leukopenia, leucocytosis

7 DRUG INTERACTIONS

Drugs for which gastric pH can affect bioavailability

Because of its profound and long lasting inhibition of gastric acid secretion, it is theoretically possible that omeprazole may interfere with absorption of drugs where gastric pH is an important determinant of their bioavailability (e.g., ketoconazole, ampicillin esters, and iron salts). In the clinical trials, antacids were used concomitantly with the administration of omeprazole delayed-release capsules.

Drugs metabolized by cytochrome P450 (CYP)

Omeprazole can prolong the elimination of diazepam, warfarin and phenytoin, drugs that are metabolized by oxidation in the liver. There have been reports of increased INR and prothrombin time in patients receiving proton pump inhibitors, including omeprazole, and warfarin concomitantly. Increases in INR and prothrombin time may lead to abnormal bleeding and even death. Patients treated with proton pump inhibitors and warfarin may need to be monitored for increases in INR and prothrombin time.

Although in normal subjects no interaction with theophylline or propranolol was found, there have been clinical reports of interaction with other drugs metabolized via the cytochrome P450 system (e.g., cyclosporine, disulfiram, benzodiazepines). Patients should be monitored to determine if it is necessary to adjust the dosage of these drugs when taken concomitantly with omeprazole omeprazole delayed-release capsules.

Concomitant administration of omeprazole and voriconazole (a combined inhibitor of CYP2C19 and CYP3A4) resulted in more than doubling of the omeprazole exposure. Dose adjustment of omeprazole is not normally required. However, in patients with Zollinger-Ellison syndrome, who may require higher doses up to 240 mg/day, dose adjustment may be considered. When voriconazole (400 mg Q12h x 1 day, then 200 mg x 6 days) was given with omeprazole (40 mg once daily x 7 days) to healthy subjects, it significantly increased the steady-state C max and AUC0-24 of omeprazole, an average of 2 times (90% CI: 1.8, 2.6) and 4 times (90% CI: 3.3, 4.4) respectively as compared to when omeprazole was given without voriconazole.

Atazanavir

Concomitant use of atazanavir and proton pump inhibitors is not recommended. Co-administration of atazanavir with proton pump inhibitors is expected to substantially decrease atazanavir plasma concentrations and thereby reduce its therapeutic effect.

Tacrolimus

Concomitant administration of omeprazole and tacrolimus may increase the serum levels of tacrolimus.

8 USE IN SPECIFIC POPULATIONS

8.1 Pregnancy

Pregnancy Category C

Reproductive studies in rats and rabbits with omeprazole and multiple cohort studies in pregnant women with omeprazole use during the first trimester do not show an increased risk of congenital anomalies or adverse pregnancy outcomes. There are no adequate and well-controlled studies on the use of omeprazole in pregnant women. Because animal reproduction studies are not always predictive of human response, this drug should be used during pregnancy only if clearly needed. The vast majority of reported experience with omeprazole during human pregnancy is first trimester exposure and the duration of use is rarely specified, e.g., intermittent vs. chronic. An expert review of published data on experiences with omeprazole use during pregnancy by TERIS – the Teratogen Information System – concluded that therapeutic doses during pregnancy are unlikely to pose a substantial teratogenic risk (the quantity and quality of data were assessed as fair).

Three epidemiological studies compared the frequency of congenital abnormalities among infants born to women who used omeprazole during pregnancy with the frequency of abnormalities among infants of women exposed to H 2-receptor antagonists or other controls. A population-based prospective cohort epidemiological study from the Swedish Medical Birth Registry, covering approximately 99% of pregnancies, reported on 955 infants (824 exposed during the first trimester with 39 of these exposed beyond first trimester, and 131 exposed after the first trimester) whose mothers used omeprazole during pregnancy. In utero exposure to omeprazole was not associated with increased risk of any malformation (odds ratio 0.82, 95% CI 0.50-1.34), low birth weight or low Apgar score. The number of infants born with ventricular septal defects and the number of stillborn infants was slightly higher in the omeprazole-exposed infants than the expected number in the normal population. The author concluded that both effects may be random.

A retrospective cohort study reported on 689 pregnant women exposed to either H 2-blockers or omeprazole in the first trimester (134 exposed to omeprazole). The overall malformation rate was 4.4% (95% CI 3.6-5.3) and the malformation rate for first trimester exposure to omeprazole was 3.6% (95% CI 1.5-8.1). The relative risk of malformations associated with first trimester exposure to omeprazole compared with non-exposed women was 0.9 (95% CI 0.3-2.2). The study could effectively rule out a relative risk greater than 2.5 for all malformations. Rates of preterm delivery or growth retardation did not differ between the groups.

A controlled prospective observational study followed 113 women exposed to omeprazole during pregnancy (89% first trimester exposures). The reported rates of major congenital malformations was 4% for the omeprazole group, 2% for controls exposed to non-teratogens, and 2.8% in disease-paired controls (background incidence of major malformations 1-5%). Rates of spontaneous and elective abortions, preterm deliveries, gestational age at delivery, and mean birth weight did not differ between the groups. The sample size in this study has 80% power to detect a 5-fold increase in the rate of major malformation.

Several studies have reported no apparent adverse short-term effects on the infant when single dose oral or intravenous omeprazole was administered to over 200 pregnant women as premedication for cesarean section under general anesthesia.

Reproductive studies conducted with omeprazole on rats at oral doses up to 56 times the human dose and in rabbits at doses up to 56 times the human dose did not show any evidence of teratogenicity. In pregnant rabbits, omeprazole at doses about 5.5 to 56 times the human dose produced dose-related increases in embryo-lethality, fetal resorptions, and pregnancy loss. In rats treated with omeprazole at doses about 5.6 to 56 times the human dose, dose-related embryo/fetal toxicity and postnatal developmental toxicity occurred in offspring. [See Animal Toxicology and/or Pharmacology (13.2)].

8.3 Nursing Mothers

Omeprazole concentrations have been measured in breast milk of a woman following oral administration of 20 mg. The peak concentration of omeprazole in breast milk was less than 7% of the peak serum concentration. This concentration would correspond to 0.004 mg of omeprazole in 200 mL of milk. Because omeprazole is excreted in human milk, because of the potential for serious adverse reactions in nursing infants from omeprazole, and because of the potential for tumorigenicity shown for omeprazole in rat carcinogenicity studies, a decision should be made whether to discontinue nursing or to discontinue the drug, taking into account the importance of the drug to the mother.

8.4 Pediatric Use

Use of omeprazole delayed-release capsules in pediatric and adolescent patients 1 to 16 years of age for the treatment of GERD is supported by a) extrapolation of results, already included in the currently approved labeling, from adequate and well-controlled studies that supported the approval of omeprazole delayed-release capsules for adults, and b) safety and pharmacokinetic studies performed in pediatric and adolescent patients. [ See Clinical Pharmacology, Pharmacokinetics, Pediatric for pharmacokinetic information (12.3) and Dosage and Administration (2), Adverse Reactions (6.1) and Clinical Studies, (14.6)]. The safety and effectiveness of omeprazole for the treatment of GERD in patients <1 year of age have not been established. The safety and effectiveness of omeprazole delayed-release capsules for other pediatric uses have not been established.

8.5 Geriatric Use

Omeprazole was administered to over 2000 elderly individuals (≥ 65 years of age) in clinical trials in the U.S. and Europe. There were no differences in safety and effectiveness between the elderly and younger subjects. Other reported clinical experience has not identified differences in response between the elderly and younger subjects, but greater sensitivity of some older individuals cannot be ruled out.

Pharmacokinetic studies have shown the elimination rate was somewhat decreased in the elderly and bioavailability was increased. The plasma clearance of omeprazole was 250 mL/min (about half that of young volunteers) and its plasma half-life averaged one hour, about twice that of young healthy volunteers. However, no dosage adjustment is necessary in the elderly. [ See Clinical Pharmacology (12.3)]

8.6 Hepatic Impairment

Consider dose reduction, particularly for maintenance of healing of erosive esophagitis. [ See Clinical Pharmacology (12.3)]

8.7 Renal Impairment

No dosage reduction is necessary. [ See Clinical Pharmacology (12.3)]

8.8 Asian Population

Consider dose reduction, particularly for maintenance of healing of erosive esophagitis. [ See Clinical Pharmacology (12.3)]

10 OVERDOSAGE

Reports have been received of overdosage with omeprazole in humans. Doses ranged up to 2400 mg (120 times the usual recommended clinical dose). Manifestations were variable, but included confusion, drowsiness, blurred vision, tachycardia, nausea, vomiting, diaphoresis, flushing, headache, dry mouth, and other adverse reactions similar to those seen in normal clinical experience. [ See Adverse Reactions (6)] Symptoms were transient, and no serious clinical outcome has been reported when omeprazole delayed-release capsules were taken alone. No specific antidote for omeprazole overdosage is known. Omeprazole is extensively protein bound and is, therefore, not readily dialyzable. In the event of overdosage, treatment should be symptomatic and supportive.

As with the management of any overdose, the possibility of multiple drug ingestion should be considered. For current information on treatment of any drug overdose, contact a Poison Control Center at 1-800-222-1222.

Single oral doses of omeprazole at 1350, 1339, and 1200 mg/kg were lethal to mice, rats, and dogs, respectively. Animals given these doses showed sedation, ptosis, tremors, convulsions, and decreased activity, body temperature, and respiratory rate and increased depth of respiration.

11 DESCRIPTION

The active ingredient in omeprazole delayed-release capsules is a substituted benzimidazole, 5-methoxy-2-[[(4-methoxy-3, 5-dimethyl-2-pyridinyl) methyl] sulfinyl]-1 H-benzimidazole, a compound that inhibits gastric acid secretion. Its empirical formula is C17H19N3O3S, with a molecular weight of 345.42. The structural formula is:

Omeprazole is a white to off-white crystalline powder that melts with decomposition at about 155°C. It is a weak base, freely soluble in ethanol and methanol, and slightly soluble in acetone and isopropanol and very slightly soluble in water. The stability of omeprazole is a function of pH; it is rapidly degraded in acid media, but has acceptable stability under alkaline conditions.

Omeprazole delayed-release capsules are supplied as delayed-release capsules for oral administration. Each delayed-release capsule contains 40 mg of omeprazole in the form of enteric-coated granules with the following inactive ingredients: cellulose, disodium hydrogen phosphate, hydroxypropyl cellulose, hypromellose, lactose, mannitol, sodium lauryl sulfate and other ingredients. The capsule shells have the following inactive ingredients: gelatin-NF, FD&C Blue #1, FD&C Red #40, D&C Red #28, titanium dioxide, synthetic black iron oxide, isopropanol, butyl alcohol, FD&C Blue #2, D&C Red #7 Calcium Lake, and, in addition, the 40 mg capsule shells also contain D&C Yellow #10.

12 CLINICAL PHARMACOLOGY

12.1 Mechanism of Action

Omeprazole belongs to a class of antisecretory compounds, the substituted benzimidazoles, that suppress gastric acid secretion by specific inhibition of the H ^+/K^+ ATPase enzyme system at the secretory surface of the gastric parietal cell. Because this enzyme system is regarded as the acid (proton) pump within the gastric mucosa, omeprazole has been characterized as a gastric acid-pump inhibitor, in that it blocks the final step of acid production. This effect is dose-related and leads to inhibition of both basal and stimulated acid secretion irrespective of the stimulus. Animal studies indicate that after rapid disappearance from plasma, omeprazole can be found within the gastric mucosa for a day or more.

12.2 Pharmacodynamics

Antisecretory Activity

After oral administration, the onset of the antisecretory effect of omeprazole occurs within one hour, with the maximum effect occurring within two hours. Inhibition of secretion is about 50% of maximum at 24 hours and the duration of inhibition lasts up to 72 hours. The antisecretory effect thus lasts far longer than would be expected from the very short (less than one hour) plasma half-life, apparently due to prolonged binding to the parietal H ^+/K^+ ATPase enzyme. When the drug is discontinued, secretory activity returns gradually, over 3 to 5 days. The inhibitory effect of omeprazole on acid secretion increases with repeated once-daily dosing, reaching a plateau after four days.

Results from numerous studies of the antisecretory effect of multiple doses of 20 mg and 40 mg of omeprazole in normal volunteers and patients are shown below. The “max” value represents determinations at a time of maximum effect (2-6 hours after dosing), while “min” values are those 24 hours after the last dose of omeprazole.

Table 1

Range of Mean Values from Multiple Studies of the Mean Antisecretory Effects of Omeprazole After Multiple Daily Dosing
 | Omeprazole 20 mg |  | Omeprazole 40 mg
Parameter | Max | Min | Max | Min
% Decrease in Basal Acid Output | 78* | 58–80 | 94* | 80–93
% Decrease in Peak Acid Output | 79* | 50–59 | 88* | 62–68
% Decrease in 24–hr Intragastric Acidity |  | 80–97 |  | 92–94
* Single Studies

Single daily oral doses of omeprazole ranging from a dose of 10 mg to 40 mg have produced 100% inhibition of 24-hour intragastric acidity in some patients.

Serum Gastrin Effects

In studies involving more than 200 patients, serum gastrin levels increased during the first 1 to 2 weeks of once-daily administration of therapeutic doses of omeprazole in parallel with inhibition of acid secretion. No further increase in serum gastrin occurred with continued treatment. In comparison with histamine H 2-receptor antagonists, the median increases produced by 20 mg doses of omeprazole were higher (1.3 to 3.6 fold vs. 1.1 to 1.8 fold increase). Gastrin values returned to pretreatment levels, usually within 1 to 2 weeks after discontinuation of therapy.

Enterochromaffin-like (ECL) Cell Effects

Human gastric biopsy specimens have been obtained from more than 3000 patients treated with omeprazole in long-term clinical trials. The incidence of ECL cell hyperplasia in these studies increased with time; however, no case of ECL cell carcinoids, dysplasia, or neoplasia has been found in these patients. [ See Clinical Pharmacology (12)] However, these studies are of insufficient duration and size to rule out the possible influence of long-term administration of omeprazole on the development of any premalignant or malignant conditions.

Other Effects

Systemic effects of omeprazole in the CNS, cardiovascular and respiratory systems have not been found to date. Omeprazole, given in oral doses of 30 or 40 mg for 2 to 4 weeks, had no effect on thyroid function, carbohydrate metabolism, or circulating levels of parathyroid hormone, cortisol, estradiol, testosterone, prolactin, cholecystokinin or secretin.

No effect on gastric emptying of the solid and liquid components of a test meal was demonstrated after a single dose of omeprazole 90 mg. In healthy subjects, a single I.V. dose of omeprazole (0.35 mg/kg) had no effect on intrinsic factor secretion. No systematic dose-dependent effect has been observed on basal or stimulated pepsin output in humans.

However, when intragastric pH is maintained at 4.0 or above, basal pepsin output is low, and pepsin activity is decreased.

As do other agents that elevate intragastric pH, omeprazole administered for 14 days in healthy subjects produced a significant increase in the intragastric concentrations of viable bacteria. The pattern of the bacterial species was unchanged from that commonly found in saliva. All changes resolved within three days of stopping treatment.

The course of Barrett’s esophagus in 106 patients was evaluated in a U.S. double-blind controlled study of omeprazole delayed-release capsules 40 mg twice daily for 12 months followed by 20 mg twice daily for 12 months or ranitidine 300 mg twice daily for 24 months. No clinically significant impact on Barrett’s mucosa by antisecretory therapy was observed. Although neosquamous epithelium developed during antisecretory therapy, complete elimination of Barrett’s mucosa was not achieved. No significant difference was observed between treatment groups in development of dysplasia in Barrett’s mucosa and no patient developed esophageal carcinoma during treatment. No significant differences between treatment groups were observed in development of ECL cell hyperplasia, corpus atrophic gastritis, corpus intestinal metaplasia, or colon polyps exceeding 3 mm in diameter [s ee Clinical Pharmacology (12)].

12.3 Pharmacokinetics

Absorption

Omeprazole delayed-release capsules contain an enteric-coated granule formulation of omeprazole (because omeprazole is acid-labile), so that absorption of omeprazole begins only after the granules leave the stomach. Absorption is rapid, with peak plasma levels of omeprazole occurring within 0.5 to 3.5 hours. Peak plasma concentrations of omeprazole and AUC are approximately proportional to doses up to 40 mg, but because of a saturable first-pass effect, a greater than linear response in peak plasma concentration and AUC occurs with doses greater than 40 mg. Absolute bioavailability (compared with intravenous administration) is about 30-40% at doses of 20-40 mg, due in large part to presystemic metabolism. In healthy subjects the plasma half-life is 0.5 to 1 hour, and the total body clearance is 500-600 mL/min.

The bioavailability of omeprazole increases slightly upon repeated administration of omeprazole delayed-release capsules.

Omeprazole delayed-release capsules 40 mg were bioequivalent when administered with and without applesauce. However, omeprazole delayed-release capsules 20 mg were not bioequivalent when administered with and without applesauce. When administered with applesauce, a mean 25% reduction in C max was observed without a significant change in AUC for omeprazole delayed-release capsules 20 mg. The clinical relevance of this finding is unknown.

Distribution

Protein binding is approximately 95%.

Metabolism

Omeprazole is extensively metabolized by the cytochrome P450 (CYP) enzyme system.

Excretion

Following single dose oral administration of a buffered solution of omeprazole, little if any unchanged drug was excreted in urine. The majority of the dose (about 77%) was eliminated in urine as at least six metabolites. Two were identified as hydroxyomeprazole and the corresponding carboxylic acid. The remainder of the dose was recoverable in feces. This implies a significant biliary excretion of the metabolites of omeprazole. Three metabolites have been identified in plasma — the sulfide and sulfone derivatives of omeprazole, and hydroxyomeprazole. These metabolites have very little or no antisecretory activity.

Combination Therapy with Antimicrobials

Omeprazole 40 mg daily was given in combination with clarithromycin 500 mg every 8 hours to healthy adult male subjects. The steady state plasma concentrations of omeprazole were increased (C max, AUC0-24, and T1/2 increases of 30%, 89% and 34% respectively) by the concomitant administration of clarithromycin. The observed increases in omeprazole plasma concentration were associated with the following pharmacological effects. The mean 24-hour gastric pH value was 5.2 when omeprazole was administered alone and 5.7 when co-administered with clarithromycin.

The plasma levels of clarithromycin and 14-hydroxy-clarithromycin were increased by the concomitant administration of omeprazole. For clarithromycin, the mean C max was 10% greater, the mean Cmin was 27% greater, and the mean AUC0-8 was 15% greater when clarithromycin was administered with omeprazole than when clarithromycin was administered alone. Similar results were seen for 14-hydroxy-clarithromycin, the mean Cmax was 45% greater, the mean Cmin was 57% greater, and the mean AUC0-8 was 45% greater. Clarithromycin concentrations in the gastric tissue and mucus were also increased by concomitant administration of omeprazole.

Table 2

Clarithromycin Tissue Concentrations 2 hours after Dose^1
Tissue | Clarithromycin | Clarithromycin + Omeprazole
Antrum | 10.48 ± 2.01 (n = 5) | 19.96 ± 4.71 (n = 5)
Fundus | 20.81 ± 7.64 (n = 5) | 24.25 ± 6.37 (n = 5)
Mucus | 4.15 ± 7.74 (n = 4) | 39.29 ± 32.79 (n = 4)
^1 Mean ± SD (µg/g)

Special Populations

Geriatric Population

The elimination rate of omeprazole was somewhat decreased in the elderly, and bioavailability was increased. Omeprazole was 76% bioavailable when a single 40 mg oral dose of omeprazole (buffered solution) was administered to healthy elderly volunteers, versus 58% in young volunteers given the same dose. Nearly 70% of the dose was recovered in urine as metabolites of omeprazole and no unchanged drug was detected. The plasma clearance of omeprazole was 250 mL/min (about half that of young volunteers) and its plasma half-life averaged one hour, about twice that of young healthy volunteers.

Pediatric Use

The pharmacokinetics of omeprazole have been investigated in pediatric patients 2 to 16 years of age:

Table 3

Pharmacokinetic Parameters of Omeprazole Following Single and Repeated Oral Administration in Pediatric Populations Compared with Adults
Single or Repeated Oral Dosing /Parameter | Children† ≤ 20 kg 2-5 years | Children† > 20 kg 6-16 years | Adults‡ mean 76 kg) 23-29 years(n = 12)
 | 10 mg | 20 mg
Single Dosing
Cmax*(ng/mL) | 288 (n = 10) | 495 (n = 49) | 668
AUC*(ng h/mL) | 511 (n = 7) | 1140 (n = 32) | 1220
Repeated Dosing
Cmax*(ng/mL) | 539 (n = 4) | 851 (n = 32) | 1458
AUC*(ng h/mL) | 1179 (n = 2) | 2276 (n = 23) | 3352

Note: * = plasma concentration adjusted to an oral dose of 1 mg/kg.

† Data from single and repeated dose studies

‡ Data from a single and repeated dose study

Doses of 10, 20 and 40 mg omeprazole as enteric-coated granules

Following comparable mg/kg doses of omeprazole, younger children (2 to 5 years of age) have lower AUCs than children 6 to 16 years of age or adults; AUCs of the latter two groups did not differ. [ See Dosage and Administration (2)]

Hepatic Impairment

In patients with chronic hepatic disease, the bioavailability increased to approximately 100% compared with an I.V. dose, reflecting decreased first-pass effect, and the plasma half-life of the drug increased to nearly 3 hours compared with the half-life in normals of 0.5-1 hour. Plasma clearance averaged 70 mL/min, compared with a value of 500-600 mL/min in normal subjects. Dose reduction, particularly where maintenance of healing of erosive esophagitis is indicated, for the hepatically impaired should be considered.

Renal Impairment

In patients with chronic renal impairment, whose creatinine clearance ranged between 10 and 62 mL/min/1.73 m ^2, the disposition of omeprazole was very similar to that in healthy volunteers, although there was a slight increase in bioavailability. Because urinary excretion is a primary route of excretion of omeprazole metabolites, their elimination slowed in proportion to the decreased creatinine clearance. No dose reduction is necessary in patients with renal impairment.

Asian Population

In pharmacokinetic studies of single 20 mg omeprazole doses, an increase in AUC of approximately four-fold was noted in Asian subjects compared with Caucasians. Dose reduction, particularly where maintenance of healing of erosive esophagitis is indicated, for Asian subjects should be considered.

12.4 Microbiology Information in H. pylori

Omeprazole and clarithromycin dual therapy and omeprazole, clarithromycin and amoxicillin triple therapy have been shown to be active against most strains of Helicobacter pylori in vitro and in clinical infections as described in the Indications and Usage section (1.1).

Helicobacter

Helicobacter pylori- Pretreatment Resistance

Clarithromycin pretreatment resistance rates were 3.5% (4/113) in the omeprazole/clarithromycin dual therapy studies (4 and 5) and 9.3% (41/439) in omeprazole/clarithromycin/amoxicillin triple therapy studies (1, 2, and 3).

Amoxicillin pretreatment susceptible isolates (≤ 0.25 µg/mL) were found in 99.3% (436/439) of the patients in the omeprazole/clarithromycin/amoxicillin triple therapy studies (1, 2, and 3). Amoxicillin pretreatment minimum inhibitory concentrations (MICs) > 0.25 µg/mL occurred in 0.7% (3/439) of the patients, all of whom were in the clarithromycin and amoxicillin study arm. One patient had an unconfirmed pretreatment amoxicillin minimum inhibitory concentration (MIC) of > 256 µg/mL by Etest ®.

Table 4

Clarithromycin Susceptibility Test Results and Clinical/Bacteriological Outcomes
Clarithromycin Susceptibility Test Results and Clinical/Bacteriological Outcomes
Clarithromycin Pretreatment Results |  |  | Clarithromycin Post-treatment Results
 | H. pylori negative – eradicated | H. pylori positive – not eradicated Post-treatment susceptibility results
 | H. pylori negative – eradicated | Sb | Ib | Rb | No MIC
Dual Therapy – (omeprazole 40 mg once daily/clarithromycin 500 three times daily for 14 days followed by omeprazole 20 mg once daily for another 14 days) (Studies 4, 5)
Susceptibleb 108 | 72 | 1 |  | 26 | 9
Intermediateb1 |  |  |  | 1
Resistantb 4 |  |  |  | 4
Triple Therapy – (omeprazole 20 mg twice daily/clarithromycin 500 mg twice daily/amoxicillin 1 g twice daily for 10 days – Studies 1, 2, 3; followed by omeprazole 20 mg once daily for another 18 days – Studies 1, 2)
Susceptibleb 171 | 153 | 7 |  | 3 | 8
Intermediateb
Resistantb 14 | 4 | 1 |  | 6 | 3
a Includes only patients with pretreatment clarithromycin susceptibility test results
b Susceptible (S) MIC ≤ 0.25 μg/mL, Intermediate (I) MIC 0.5 – 1.0 μg/mL, Resistant (R) MIC ≥ 2 μg/mL

Patients not eradicated of H. pylori following omeprazole/clarithromycin/amoxicillin triple therapy or omeprazole/clarithromycin dual therapy will likely have clarithromycin resistant H. pylori isolates. Therefore, clarithromycin susceptibility testing should be done, if possible. Patients with clarithromycin resistant H. pylori should not be treated with any of the following: omeprazole/clarithromycin dual therapy, omeprazole/clarithromycin/amoxicillin triple therapy, or other regimens which include clarithromycin as the sole antimicrobial agent.

Amoxicillin Susceptibility Test Results and Clinical/Bacteriological Outcomes

In the triple therapy clinical trials, 84.9% (157/185) of the patients in the omeprazole/clarithromycin/amoxicillin treatment group who had pretreatment amoxicillin susceptible MICs (≤ 0.25 µg/mL) were eradicated of H. pylori and 15.1% (28/185) failed therapy. Of the 28 patients who failed triple therapy, 11 had no post-treatment susceptibility test results and 17 had post-treatment H. pylori isolates with amoxicillin susceptible MICs. Eleven of the patients who failed triple therapy also had post-treatment H. pylori isolates with clarithromycin resistant MICs.

Susceptibility Test for Helicobacter pylori

The reference methodology for susceptibility testing of H. pylori is agar dilution MICs^1. One to three microliters of an inoculum equivalent to a No. 2 McFarland standard (1 x 10^7 - 1 x 10^8 CFU/mL for H. pylori) are inoculated directly onto freshly prepared antimicrobial containing Mueller-Hinton agar plates with 5% aged defibrinated sheep blood (≥ 2 weeks old). The agar dilution plates are incubated at 35°C in a microaerobic environment produced by a gas generating system suitable for campylobacters. After 3 days of incubation, the MICs are recorded as the lowest concentration of antimicrobial agent required to inhibit growth of the organism. The clarithromycin and amoxicillin MIC values should be interpreted according to the following criteria:

Table 5

Clarithromycin MIC (µg/mL)a | Interpretation
≤ 0.25 | Susceptible (S)
0.5 | Intermediate (I)
> 1.0 | Resistant (R)
Amoxicillin MIC (µg/mL)a,b | Interpretation
≤ 0.25 | Susceptible (S)

a These are tentative breakpoints for the agar dilution methodology and they should not be used to interpret results obtained using alternative methods.

b There were not enough organisms with MICs > 0.25 µg/mL to determine a resistance breakpoint.

Standardized susceptibility test procedures require the use of laboratory control microorganisms to control the technical aspects of the laboratory procedures. Standard clarithromycin and amoxicillin powders should provide the following MIC values:

Microorganism | Antimicrobial Agent | MIC (µg/mL)a
H. pylori ATCC 43504 | Clarithromycin | 0.016- 0.12 (µg/mL)
H. pylori ATCC 43504 | Amoxicillin | 0.016- 0.12 (µg/mL)

a These are quality control ranges for the agar dilution methodology and they should not be used to control test results obtained using alternative methods.

13 NONCLINICAL TOXICOLOGY

13.1 Carcinogenesis, Mutagenesis, Impairment of Fertility

In two 24-month carcinogenicity studies in rats, omeprazole at daily doses of 1.7, 3.4, 13.8, 44.0 and 140.8 mg/kg/day (about 0.7 to 57 times a human dose of 20 mg/day, as expressed on a body surface area basis) produced gastric ECL cell carcinoids in a dose-related manner in both male and female rats; the incidence of this effect was markedly higher in female rats, which had higher blood levels of omeprazole. Gastric carcinoids seldom occur in the untreated rat. In addition, ECL cell hyperplasia was present in all treated groups of both sexes. In one of these studies, female rats were treated with 13.8 mg omeprazole/kg/day (about 6 times a human dose of 20 mg/day, based on body surface area) for one year, and then followed for an additional year without the drug. No carcinoids were seen in these rats. An increased incidence of treatment-related ECL cell hyperplasia was observed at the end of one year (94% treated vs 10% controls). By the second year the difference between treated and control rats was much smaller (46% vs 26%) but still showed more hyperplasia in the treated group. Gastric adenocarcinoma was seen in one rat (2%). No similar tumor was seen in male or female rats treated for two years. For this strain of rat no similar tumor has been noted historically, but a finding involving only one tumor is difficult to interpret. In a 52-week toxicity study in Sprague-Dawley rats, brain astrocytomas were found in a small number of males that received omeprazole at dose levels of 0.4, 2, and 16 mg/kg/day (about 0.2 to 6.5 times the human dose on a body surface area basis). No astrocytomas were observed in female rats in this study. In a 2-year carcinogenicity study in Sprague-Dawley rats, no astrocytomas were found in males or females at the high dose of 140.8 mg/kg/day (about 57 times the human dose on a body surface area basis). A 78-week mouse carcinogenicity study of omeprazole did not show increased tumor occurrence, but the study was not conclusive. A 26-week p53 (+/-) transgenic mouse carcinogenicity study was not positive.

Omeprazole was positive for clastogenic effects in an in vitro human lymphocyte chromosomal aberration assay, in one of two in vivo mouse micronucleus tests, and in an in vivo bone marrow cell chromosomal aberration assay. Omeprazole was negative in the in vitro Ames test, an in vitro mouse lymphoma cell forward mutation assay, and an in vivo rat liver DNA damage assay.

Omeprazole at oral doses up to 138 mg/kg/day in rats (about 56 times the human dose on a body surface area basis) was found to have no effect on fertility and reproductive performance.

In 24-month carcinogenicity studies in rats, a dose-related significant increase in gastric carcinoid tumors and ECL cell hyperplasia was observed in both male and female animals [ See Warnings and Precautions (5)] Carcinoid tumors have also been observed in rats subjected to fundectomy or long-term treatment with other proton pump inhibitors or high doses of H2-receptor antagonists.

13.2 Animal Toxicology and/or Pharmacology

Reproductive Toxicology Studies

Reproductive studies conducted with omeprazole in rats at oral doses up to 138 mg/kg/day (about 56 times the human dose on a body surface area basis) and in rabbits at doses up to 69 mg/kg/day (about 56 times the human dose on a body surface area basis) did not disclose any evidence for a teratogenic potential of omeprazole. In rabbits, omeprazole in a dose range of 6.9 to 69.1 mg/kg/day (about 5.5 to 56 times the human dose on a body surface area basis) produced dose-related increases in embryo-lethality, fetal resorptions, and pregnancy disruptions. In rats, dose-related embryo/fetal toxicity and postnatal developmental toxicity were observed in offspring resulting from parents treated with omeprazole at 13.8 to 138.0 mg/kg/day (about 5.6 to 56 times the human doses on a body surface area basis).

14 CLINICAL STUDIES

14.1 Duodenal Ulcer Disease

Active Duodenal Ulcer— In a multicenter, double-blind, placebo-controlled study of 147 patients with endoscopically documented duodenal ulcer, the percentage of patients healed (per protocol) at 2 and 4 weeks was significantly higher with omeprazole delayed-release capsules 20 mg once daily than with placebo (p ≤ 0.01).

Treatment of Active Duodenal Ulcer % of Patients Healed
 | Omeprazole delayed-release capsules 20 mg a.m. | Placebo a.m.
 | (n = 99) | (n = 48)
Week 2 | *41 | 13
Week 4 | *75 | 27

* (p ≤ 0.01)

Complete daytime and nighttime pain relief occurred significantly faster (p ≤ 0.01) in patients treated with omeprazole delayed-release capsules 20 mg than in patients treated with placebo. At the end of the study, significantly more patients who had received omeprazole delayed-release capsules had complete relief of daytime pain (p ≤ 0.05) and nighttime pain (p ≤ 0.01).

In a multicenter, double-blind study of 293 patients with endoscopically documented duodenal ulcer, the percentage of patients healed (per protocol) at 4 weeks was significantly higher with omeprazole delayed-release capsules 20 mg once daily than with ranitidine 150 mg b.i.d. (p < 0.01).

Treatment of Active Duodenal Ulcer % of Patients Healed
 | Omeprazole delayed-release capsules 20 mg | Ranitidine
 | 20 mg a.m. | 150 mg twice daily
 | (n = 145) | (n = 148)
Week 2 | 42 | 34
Week 4 | *82 | 63

* (p < 0.01)

Healing occurred significantly faster in patients treated with omeprazole delayed-release capsules than in those treated with ranitidine 150 mg b.i.d. (p < 0.01).

In a foreign multinational randomized, double-blind study of 105 patients with endoscopically documented duodenal ulcer, 20 mg and 40 mg of omeprazole delayed-release capsules were compared with 150 mg b.i.d. of ranitidine at 2, 4 and 8 weeks. At 2 and 4 weeks both doses of omeprazole delayed-release capsules were statistically superior (per protocol) to ranitidine, but 40 mg was not superior to 20 mg of omeprazole delayed-release capsules, and at 8 weeks there was no significant difference between any of the active drugs.

Treatment of Active Duodenal Ulcer % of Patients Healed
 | Omeprazole delayed-release capsules |  | Ranitidine
 | 20 mg (n = 34) | 40 mg (n = 36) | 150 mg twice daily (n = 35)
Week 2 | *83 | *83 | 53
Week 4 | *97 | *100 | 82
Week 8 | 100 | 100 | 94

* (p ≤ 0.01)

H. pylori Eradication in Patients with Duodenal Ulcer Disease

Triple Therapy (omeprazole delayed-release capsules/clarithromycin/amoxicillin)

Three U.S., randomized, double-blind clinical studies in patients with H. pylori infection and duodenal ulcer disease (n = 558) compared omeprazole delayed-release capsules plus clarithromycin plus amoxicillin with clarithromycin plus amoxicillin. Two studies (1 and 2) were conducted in patients with an active duodenal ulcer, and the other study (3) was conducted in patients with a history of a duodenal ulcer in the past 5 years but without an ulcer present at the time of enrollment. The dose regimen in the studies was omeprazole 20 mg twice daily plus clarithromycin 500 mg twice daily plus amoxicillin 1 g twice daily for 10 days; or clarithromycin 500 mg twice daily plus amoxicillin 1 g twice daily for 10 days. In studies 1 and 2, patients who took the omeprazole regimen also received an additional 18 days of omeprazole delayed-release capsules 20 mg once daily. Endpoints studied were eradication of H. pylori and duodenal ulcer healing (studies 1 and 2 only). H. pylori status was determined by CLOtest®, histology and culture in all three studies. For a given patient, H. pylori was considered eradicated if at least two of these tests were negative, and none was positive.

The combination of omeprazole plus clarithromycin plus amoxicillin was effective in eradicating H. pylori.

Table 6

Per-Protocol and Intent-to-Treat H. pylori Eradication Rates % of Patients Cured [95% Confidence Interval]
 | Omeprazole delayed-release capsules + clarithromycin + amoxicillin |  | Clarithroycin +amoxicillin
 | Per-Protocol† | Intent-to-Treat‡ | Per-Protocol† | Intent-to-Treat‡
Study 1 | *77 [64, 86](n = 64) | *69 [57, 79](n = 80) | 43 [31, 56](n = 67) | 37 [27, 48](n = 84)
Study 2 | *78 [67, 88] (n = 65) | *73 [61, 82] (n = 77) | 41 [29, 54](n = 68) | 36 [26, 47](n = 83)
Study 3 | *90 [80, 96] (n = 69) | *83 [74, 91] (n = 84) | 33 [24, 44](n = 93) | 32 [23, 42](n = 99)

† Patients were included in the analysis if they had confirmed duodenal ulcer disease (active ulcer, studies 1 and 2; history of ulcer within 5 years, study 3) and H. pylori infection at baseline defined as at least two of three positive endoscopic tests from CLOtest®, histology, and/or culture. Patients were included in the analysis if they completed the study. Additionally, if patients dropped out of the study due to an adverse event related to the study drug, they were included in the analysis as failures of therapy. The impact of eradication on ulcer recurrence has not been assessed in patients with a past history of ulcer.

‡ Patients were included in the analysis if they had documented H. pylori infection at baseline and had confirmed duodenal ulcer disease. All dropouts were included as failures of therapy.

* (p < 0.05) versus clarithromycin plus amoxicillin.

Dual Therapy (omeprazole delayed-release capsules/clarithromycin)

Four randomized, double-blind, multi-center studies (4, 5, 6, and 7) evaluated omeprazole delayed-release capsules 40 mg once daily plus clarithromycin 500 mg three times daily for 14 days, followed by omeprazole delayed-release capsules 20 mg once daily, (Studies 4, 5, and 7) or by omeprazole delayed-release capsules 40 mg once daily (Study 6) for an additional 14 days in patients with active duodenal ulcer associated with H. pylori. Studies 4 and 5 were conducted in the U.S. and Canada and enrolled 242 and 256 patients, respectively. H. pylori infection and duodenal ulcer were confirmed in 219 patients in Study 4 and 228 patients in Study 5. These studies compared the combination regimen to omeprazole delayed-release capsules and clarithromycin monotherapies. Studies 6 and 7 were conducted in Europe and enrolled 154 and 215 patients, respectively. H. pylori infection and duodenal ulcer were confirmed in 148 patients in study 6 and 208 patients in Study 7. These studies compared the combination regimen with omeprazole monotherapy. The results for the efficacy analyses for these studies are described below. H. pylori eradication was defined as no positive test (culture or histology) at 4 weeks following the end of treatment, and two negative tests were required to be considered eradicated of H. pylori. In the per-protocol analysis, the following patients were excluded: dropouts, patients with missing H. pylori tests post-treatment, and patients that were not assessed for H. pylori eradication because they were found to have an ulcer at the end of treatment.

The combination of omeprazole and clarithromycin was effective in eradicating H. pylori.

Table 7

H. pylori Eradication Rates (Per-Protocol Analysis at 4 to 6 Weeks) % of Patients Cured [95% Confidence Interval]
 | Omeprazole delayed-release capsules +Clarithromycin | Omeprazole delayed-release capsules | Clarithromycin
U.S. Studies
Study 4 | 74 [60, 85]†‡ (n = 53) | 0 [0, 7](n = 54) | 31 [18, 47](n = 42)
Study 5 | 64 [51, 76]†‡(n = 61) | 0 [0, 6](n = 59) | 39 [24, 55](n =44)
Non U.S. Studies
Study 6 | 83 [71, 92]‡(n = 60) | 1[0, 7](n = 74) | N/A
Study 7 | 74 [64, 83]‡(n = 86) | 1[0, 6](n = 90) | N/A

† Statistically significantly higher than clarithromycin monotherapy (p < 0.05)

‡ Statistically significantly higher than omeprazole monotherapy (p < 0.05)

Ulcer healing was not significantly different when clarithromycin was added to omeprazole therapy compared with omeprazole therapy alone.

The combination of omeprazole and clarithromycin was effective in eradicating H. pylori and reduced duodenal ulcer recurrence.

Table 8

Duodenal Ulcer Recurrence Rates by H. pylori Eradication Status % of Patients with Ulcer Recurrence
 | H. pylori eradicated# | H. pylori not eradicated#
U.S. Studies† 6 months post-treatment
Study 4 | *35 (n = 49) | 60 (n = 88)
Study 5 | *8 (n = 53) | 60 (n = 106)
Non U.S. Studies‡ 6 months post-treatment
Study 6 | *5 (n = 43) | 46 (n = 78)
Study 7 | *6 (n = 53) | 43 (n = 107)
12 months post-treatment
Study 6 | *5 (n = 39) | 68 (n = 71)

# H. pylori eradication status assessed at same time point as ulcer recurrence

† Combined results for omeprazole delayed-release capsules + clarithromycin, omeprazole delayed-release capsules, and clarithromycin treatment arms

‡ Combined results for omeprazole delayed-release capsules + clarithromycin and omeprazole delayed-release capsules treatment arms

* (p ≤ 0.01) versus proportion with duodenal ulcer recurrence who were not H. pylori eradicated

14.2 Gastric Ulcer

In a U.S. multicenter, double-blind, study of omeprazole 40 mg once daily, 20 mg once daily, and placebo in 520 patients with endoscopically diagnosed gastric ulcer, the following results were obtained.

Treatment of Gastric Ulcer% of Patients Healed (All Patients Treated)
 | Omeprazole delayed-release capsules 20 mg once daily (n = 202) | Omeprazole delayed-release capsules 40 mg once daily (n = 214) | Placebo (n = 104)
Week 4 | 47.5** | 55.6** | 30.8
Week 8 | 74.8** | 82.7**,+ | 48.1

** (p < 0.01) omeprazole delayed-release capsules 40 mg or 20 mg versus placebo

^+ (p < 0.05) omeprazole delayed-release capsules 40 mg versus 20 mg

For the stratified groups of patients with ulcer size less than or equal to 1 cm, no difference in healing rates between 40 mg and 20 mg was detected at either 4 or 8 weeks. For patients with ulcer size greater than 1 cm, 40 mg was significantly more effective than 20 mg at 8 weeks.

In a foreign, multinational, double-blind study of 602 patients with endoscopically diagnosed gastric ulcer, omeprazole 40 mg once daily, 20 mg once daily, and ranitidine 150 mg twice a day were evaluated.

Treatment of Gastric Ulcer% of Patients Healed (All Patients Treated)
 | Omeprazole delayed-release capsules 20 mg once daily (n = 200) | Omeprazole delayed-release capsule 40 mg once daily (n = 187) | Ranitidine150 mg twice daily (n = 199)
Week 4 | 63.5 | 78.1**,++ | 56.3
Week 8 | 81.5 | 91.4**,++ | 78.4

** (p < 0.01) omeprazole delayed-release capsules 40 mg versus ranitidine

^++ (p < 0.01) omeprazole delayed-release capsules 40 mg versus 20 mg

14.3 Gastroesophageal Reflux Disease (GERD)

Symptomatic GERD

A placebo-controlled study was conducted in Scandinavia to compare the efficacy of omeprazole 20 mg or 10 mg once daily for up to 4 weeks in the treatment of heartburn and other symptoms in GERD patients without erosive esophagitis. Results are shown below.

% Successful Symptomatic Outcomea
 | Omeprazole delayed-release capsules 20 mg a.m. | Omeprazole delayed-release capsules 10 mg a.m. | PLACEBO a.m.
All patients | 46*,†(n = 205) | 31†(n = 199) | 13(n = 105)
Patients with confirmed GERD | 56*,†(n = 115) | 36†(n = 109) | 14(n = 59)

a Defined as complete resolution of heartburn

* (p < 0.005) versus 10 mg

† (p < 0.005) versus placebo

14.4 Erosive Esophagitis

In a U.S. multicenter double-blind placebo controlled study of 20 mg or 40 mg of omeprazole delayed-release capsules in patients with symptoms of GERD and endoscopically diagnosed erosive esophagitis of grade 2 or above, the percentage healing rates (per protocol) were as follows:

 | 20 mg Omeprazole delayed-release capsules (n = 83) | 40 mg Omeprazole delayed-release capsule (n = 87) | Placebo(n = 43)
Week 4 | 39 ** | 45** | 7
Week 8 | 74** | 75** | 14

** (p < 0.01) omeprazole delayed-release capsules versus placebo.

In this study, the 40 mg dose was not superior to the 20 mg dose of omeprazole delayed-release capsules in the percentage healing rate. Other controlled clinical trials have also shown that omeprazole delayed-release capsules are effective in severe GERD. In comparisons with histamine H 2-receptor antagonists in patients with erosive esophagitis, grade 2 or above, omeprazole delayed-release capsules in a dose of 20 mg was significantly more effective than the active controls. Complete daytime and nighttime heartburn relief occurred significantly faster (p < 0.01) in patients treated with omeprazole delayed-release capsules than in those taking placebo or histamine H2- receptor antagonists.

In this and five other controlled GERD studies, significantly more patients taking 20 mg omeprazole (84%) reported complete relief of GERD symptoms than patients receiving placebo (12%).

Long Term Maintenance Of Healing of Erosive Esophagitis

In a U.S. double-blind, randomized, multicenter, placebo controlled study, two dose regimens of omeprazole were studied in patients with endoscopically confirmed healed esophagitis. Results to determine maintenance of healing of erosive esophagitis are shown below.

Life Table Analysis
 | Omeprazole delayed-release capsules 20 mg once daily (n = 138) | Omeprazole delayed-release capsules 20 mg 3 days per week (n = 137) | Placebo (n = 131)
Percent in endoscopic remission at 6 months | *70 | 34 | 11

* (p < 0.01) omeprazole delayed-release capsules 20 mg once daily versus omeprazole delayed-release capsules 20 mg 3 consecutive days per week or placebo.

In an international multicenter double-blind study, omeprazole delayed-release capsules 20 mg daily and 10 mg daily were compared with ranitidine 150 mg twice daily in patients with endoscopically confirmed healed esophagitis. The table below provides the results of this study for maintenance of healing of erosive esophagitis.

Life Table Analysis
 | Omeprazole delayed-release capsules 20 mg once daily (n = 131) | Omeprazole10 mg once daily (n = 133) | Ranitidine150 mg twice daily (n = 128)
Percent in endoscopic remission at 12 months | *77 | ‡58 | 46

* (p = 0.01) omeprazole delayed-release capsules 20 mg once daily versus omeprazole delayed-release capsules 10 mg once daily or Ranitidine.

‡ (p = 0.03) omeprazole delayed-release capsules 10 mg once daily versus Ranitidine.

In patients who initially had grades 3 or 4 erosive esophagitis, for maintenance after healing 20 mg daily of omeprazole delayed-release capsules was effective, while 10 mg did not demonstrate effectiveness.

14.5 Pathological Hypersecretory Conditions

In open studies of 136 patients with pathological hypersecretory conditions, such as Zollinger-Ellison (ZE) syndrome with or without multiple endocrine adenomas, omeprazole delayed-release capsules significantly inhibited gastric acid secretion and controlled associated symptoms of diarrhea, anorexia, and pain. Doses ranging from 20 mg every other day to 360 mg per day maintained basal acid secretion below 10 mEq/hr in patients without prior gastric surgery, and below 5 mEq/hr in patients with prior gastric surgery.

Initial doses were titrated to the individual patient need, and adjustments were necessary with time in some patients [ See Dosage and Administration (2)] omeprazole delayed-release capsules were well tolerated at these high dose levels for prolonged periods (> 5 years in some patients). In most ZE patients, serum gastrin levels were not modified by omeprazole delayed-release capsule. However, in some patients serum gastrin increased to levels greater than those present prior to initiation of omeprazole therapy. At least 11 patients with ZE syndrome on long-term treatment with omeprazole delayed-release capsules developed gastric carcinoids. These findings are believed to be a manifestation of the underlying condition, which is known to be associated with such tumors, rather than the result of the administration of omeprazole delayed-release capsules. [See Adverse Reactions (6)]

14.6 Pediatric GERD

Symptomatic GERD

The effectiveness of omeprazole delayed-release capsulesfor the treatment of nonerosive GERD in pediatric patients 1 to 16 years of age is based in part on data obtained from 125 pediatric patients in two uncontrolled Phase III studies. [ See Use in Specific Populations (8.4)]

The first study enrolled 12 pediatric patients 1 to 2 years of age with a history of clinically diagnosed GERD. Patients were administered a single dose of omeprazole (0.5 mg/kg, 1.0 mg/kg, or 1.5 mg/kg) for 8 weeks as an open capsule in 8.4% sodium bicarbonate solution. Seventy-five percent (9/12) of the patients had vomiting/regurgitation episodes decreased from baseline by at least 50%.

The second study enrolled 113 pediatric patients 2 to 16 years of age with a history of symptoms suggestive of nonerosive GERD. Patients were administered a single dose of omeprazole (10 mg or 20 mg, based on body weight) for 4 weeks either as an intact capsule or as an open capsule in applesauce. Successful response was defined as no moderate or severe episodes of either pain-related symptoms or vomiting/regurgitation during the last 4 days of treatment. Results showed success rates of 60% (9/15; 10 mg omeprazole) and 59% (58/98; 20 mg omeprazole), respectively.

Healing of Erosive Esophagitis

In an uncontrolled, open-label dose-titration study, healing of erosive esophagitis in pediatric patients 1 to 16 years of age required doses that ranged from 0.7 to 3.5 mg/kg/day (80 mg/day). Doses were initiated at 0.7 mg/kg/day. Doses were increased in increments of 0.7 mg/kg/day (if intraesophageal pH showed a pH of < 4 for less than 6% of a 24-hour study). After titration, patients remained on treatment for 3 months. Forty-four percent of the patients were healed on a dose of 0.7 mg/kg body weight; most of the remaining patients were healed with 1.4 mg/kg after an additional 3 months’ treatment. Erosive esophagitis was healed in 51 of 57 (90%) children who completed the first course of treatment in the healing phase of the study. In addition, after 3 months of treatment, 33% of the children had no overall symptoms, 57% had mild reflux symptoms, and 40% had less frequent regurgitation/vomiting.

Maintenance of Healing of Erosive Esophagitis

In an uncontrolled, open-label study of maintenance of healing of erosive esophagitis in 46 pediatric patients, 54% of patients required half the healing dose. The remaining patients increased the healing dose (0.7 to a maximum of 2.8 mg/kg/day) either for the entire maintenance period, or returned to half the dose before completion. Of the 46 patients who entered the maintenance phase, 19 (41%) had no relapse. In addition, maintenance therapy in erosive esophagitis patients resulted in 63% of patients having no overall symptoms.

15 REFERENCES

1. National Committee for Clinical Laboratory Standards. Methods for Dilution Antimicrobial Susceptibility Tests for Bacteria That Grow Aerobically—Fifth Edition. Approved Standard NCCLS Document M7-A5, Vol, 20, No. 2, NCCLS, Wayne, PA, January 2000.

16 HOW SUPPLIED/STORAGE AND HANDLING

Omeprazole delayed-release capsules, 40 mg, are opaque, hard gelatin, apricot and amethystcolored capsules, coded 1740 on cap and 40 mg on the body. They are supplied as follows:

NDC 63304-445-30 unit of use bottles of 30

NDC 63304-445-01 bottles of 100

NDC 63304-445-10 bottles of 1000.

Storage

Store omeprazole delayed-release capsules in a tight container protected from light and moisture. Store between 15 °C and 30°C (59°F and 86°F).

17 PATIENT COUNSELING INFORMATION

Omeprazole delayed-release capsules should be taken before eating. Patients should be informed that the omeprazole delayed-release capsule should be swallowed whole.

For patients who have difficulty swallowing capsules, the contents of an omeprazole delayed-release capsule can be added to applesauce. One tablespoon of applesauce should be added to an empty bowl and the capsule should be opened. All of the pellets inside the capsule should be carefully emptied on the applesauce. The pellets should be mixed with the applesauce and then swallowed immediately with a glass of cool water to ensure complete swallowing of the pellets. The applesauce used should not be hot and should be soft enough to be swallowed without chewing. The pellets should not be chewed or crushed. The pellets/applesauce mixture should not be stored for future use.

Manufactured for:

Ranbaxy Pharmaceuticals Inc.

Jacksonville, FL 32257, USA

By: Merck & Co., Inc.

Whitehouse Station, NJ 08889, USA

9867401

31201-01 Rev. 08/08

PACKAGING LABEL PRINCIPAL DISPLAY PANEL

40 mg / 30 capsules
40 mg / 100 capsules
40 mg / 1000 capsules